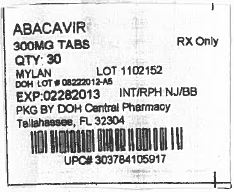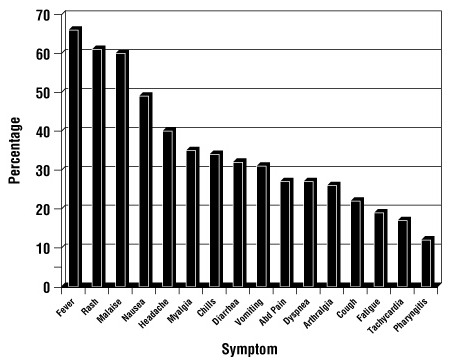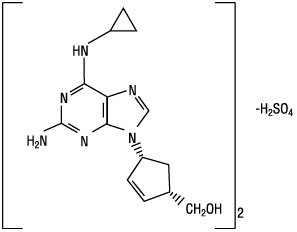 DRUG LABEL: Abacavir Sulfate
NDC: 53808-0627 | Form: TABLET, FILM COATED
Manufacturer: State of Florida DOH Central Pharmacy
Category: prescription | Type: HUMAN PRESCRIPTION DRUG LABEL
Date: 20130808

ACTIVE INGREDIENTS: ABACAVIR SULFATE 300 mg/1 1
INACTIVE INGREDIENTS: SILICON DIOXIDE; HYPROMELLOSES; MAGNESIUM STEARATE; CELLULOSE, MICROCRYSTALLINE; POLYETHYLENE GLYCOLS; FERRIC OXIDE RED; SODIUM STARCH GLYCOLATE TYPE A POTATO; TITANIUM DIOXIDE; FERRIC OXIDE YELLOW

HIGHLIGHTS OF PRESCRIBING INFORMATION

These highlights do not include all the information needed to use abacavir tablets safely and effectively. See full prescribing information for abacavir tablets.
Abacavir Tablets, USP for Oral Use
Initial U.S. Approval: 1998

RECENT MAJOR CHANGES

Dosage and Administration (2) 05/2012

Warnings and Precautions, Hypersensitivity Reaction (5.1) 05/2012

Warnings and Precautions, Immune Reconstitution Syndrome (5.3) 11/2011

WARNING: RISK OF HYPERSENSITIVITY REACTIONS, LACTIC ACIDOSIS, AND SEVERE HEPATOMEGALY

WARNING: HYPERSENSITIVITY REACTIONS, LACTIC ACIDOSIS, AND SEVERE HEPATOMEGALY

See full prescribing information for complete boxed warning.

- Serious and sometimes fatal hypersensitivity reactions have been associated with abacavir (abacavir sulfate). (5.1)
- Hypersensitivity to abacavir is a multi-organ clinical syndrome. (5.1)
- Patients who carry the HLA-B*5701 allele are at high risk for experiencing a hypersensitivity reaction to abacavir. (5.1)
- Discontinue abacavir as soon as a hypersensitivity reaction is suspected. Regardless of HLA-B*5701 status, permanently discontinue abacavir if hypersensitivity cannot be ruled out, even when other diagnoses are possible. (5.1)
- Following a hypersensitivity reaction to abacavir, NEVER restart abacavir tablets or any other abacavir-containing product. (5.1)
- Lactic acidosis and severe hepatomegaly with steatosis, including fatal cases, have been reported with the use of nucleoside analogues. (5.2)

1 INDICATIONS AND USAGE

Abacavir, a nucleoside analogue, is indicated in combination with other antiretroviral agents for the treatment of HIV-1 infection. (1)

2 DOSAGE AND ADMINISTRATION

- A medication guide and warning card should be dispensed with each new prescription and refill. (2)
- Adults: 600 mg daily, administered as either 300 mg twice daily or 600 mg once daily. (2.1)
- Pediatric Patients Aged 3 Months and Older: Dose should be calculated on body weight (kg) and should not exceed 300 mg twice daily. (2.2)
- Patients with Hepatic Impairment: Mild hepatic impairment – 200 mg twice daily; moderate/severe hepatic impairment – contraindicated. (2.3)

3 DOSAGE FORMS AND STRENGTHS

Tablets: 300 mg, scored (3)

4 CONTRAINDICATIONS

- Previously demonstrated hypersensitivity to abacavir. (4, 5.1)
- Moderate or severe hepatic impairment. (4)

5 WARNINGS AND PRECAUTIONS

- Hypersensitivity: Serious and sometimes fatal hypersensitivity reactions have been associated with abacavir tablets and other abacavir-containing products. Read full prescribing information section 5.1 before prescribing abacavir tablets. (5.1)
- Lactic acidosis and severe hepatomegaly with steatosis have been reported with the use of nucleoside analogues. (5.2)
- Immune reconstitution syndrome (5.3) and redistribution/accumulation of body fat have been reported in patients treated with combination antiretroviral therapy. (5.4)

6 ADVERSE REACTIONS

- The most commonly reported adverse reactions of at least moderate intensity (incidence ≥ 10%) in adult HIV-1 clinical trials were nausea, headache, malaise and fatigue, nausea and vomiting, and dreams/sleep disorders. (6.1)
- The most commonly reported adverse reactions of at least moderate intensity (incidence ≥ 5%) in pediatric HIV-1 clinical trials were fever and/or chills, nausea and vomiting, skin rashes, and ear/nose/throat infections. (6.1)

To report SUSPECTED ADVERSE REACTIONS, contact Mylan Pharmaceuticals Inc. at 1-877-446-3679 (1-877-4-INFO-RX) or FDA at 1-800-FDA-1088 or www.fda.gov/medwatch.

7 DRUG INTERACTIONS

- Ethanol: Decreases elimination of abacavir. (7.1)
- Methadone: An increased methadone dose may be required in a small number of patients. (7.2)

FULL PRESCRIBING INFORMATION

WARNING: RISK OF HYPERSENSITIVITY REACTIONS, LACTIC ACIDOSIS, AND SEVERE HEPATOMEGALY

Hypersensitivity Reactions: Serious and sometimes fatal hypersensitivity reactions have been associated with abacavir (abacavir sulfate).

Hypersensitivity to abacavir is a multi-organ clinical syndrome usually characterized by a sign or symptom in two or more of the following groups: (1) fever, (2) rash, (3) gastrointestinal (including nausea, vomiting, diarrhea, or abdominal pain), (4) constitutional (including generalized malaise, fatigue, or achiness), and (5) respiratory (including dyspnea, cough, or pharyngitis). Discontinue abacavir as soon as a hypersensitivity reaction is suspected.

Patients who carry the HLA-B*5701 allele are at high risk for experiencing a hypersensitivity reaction to abacavir. Prior to initiating therapy with abacavir, screening for the HLA-B*5701 allele is recommended; this approach has been found to decrease the risk of hypersensitivity reaction. Screening is also recommended prior to reinitiation of abacavir in patients of unknown HLA-B*5701 status who have previously tolerated abacavir. HLA-B*5701-negative patients may develop a suspected hypersensitivity reaction to abacavir; however, this occurs significantly less frequently than in HLA-B*5701-positive patients.

Regardless of HLA-B*5701 status, permanently discontinue abacavir if hypersensitivity cannot be ruled out, even when other diagnoses are possible. Following a hypersensitivity reaction to abacavir, NEVER restart abacavir tablets or any other abacavir-containing product because more severe symptoms can occur within hours and may include life threatening hypotension and death.

Reintroduction of abacavir tablets or any other abacavir-containing product, even in patients who have no identified history or unrecognized symptoms of hypersensitivity to abacavir therapy, can result in serious or fatal hypersensitivity reactions. Such reactions can occur within hours [see Warnings and Precautions (5.1)].

Lactic Acidosis and Severe Hepatomegaly: Lactic acidosis and severe hepatomegaly with steatosis, including fatal cases, have been reported with the use of nucleoside analogues alone or in combination, including abacavir and other antiretrovirals [see Warnings and Precautions (5.2)].

1 INDICATIONS AND USAGE

Abacavir tablets, in combination with other antiretroviral agents, are indicated for the treatment of human immunodeficiency virus (HIV-1) infection.

Additional important information on the use of abacavir tablets for treatment of HIV-1 infection:

- Abacavir tablets are one of multiple products containing abacavir. Before starting abacavir tablets, review medical history for prior exposure to any abacavir-containing product in order to avoid reintroduction in a patient with a history of hypersensitivity to abacavir [see Warnings and Precautions (5.1), Adverse Reactions (6)].

2 DOSAGE AND ADMINISTRATION

- A Medication Guide and Warning Card that provide information about recognition of hypersensitivity reactions should be dispensed with each new prescription and refill.
- Abacavir tablets may be taken with or without food.

2.1 Adult Patients

The recommended oral dose of abacavir tablets for adults is 600 mg daily, administered as either 300 mg twice daily or 600 mg once daily, in combination with other antiretroviral agents.

2.2 Pediatric Patients

The recommended oral dose of abacavir oral solution in HIV-1-infected pediatric patients aged 3 months and older is 8 mg/kg twice daily (up to a maximum of 300 mg twice daily) in combination with other antiretroviral agents.

Abacavir is also available as a scored tablet for HIV-1-infected pediatric patients weighing greater than or equal to 14 kg for whom a solid dosage form is appropriate. Before prescribing abacavir tablets, children should be assessed for the ability to swallow tablets. If a child is unable to reliably swallow abacavir tablets, the oral solution formulation should be prescribed. The recommended oral dosage of abacavir tablets for HIV-1-infected pediatric patients is presented in Table 1.

Table 1. Dosing Recommendations for Abacavir Tablets in Pediatric Patients
Weight (kg) | Dosage Regimen Using Scored Tablet |  | Total Daily Dose
Weight (kg) | AM Dose | PM Dose | Total Daily Dose
14 to 21 | ½ tablet (150 mg) | ½ tablet (150 mg) | 300 mg
> 21 to < 30 | ½ tablet (150 mg) | 1 tablet (300 mg) | 450 mg
≥ 30 | 1 tablet (300 mg) | 1 tablet (300 mg) | 600 mg

2.3 Patients with Hepatic Impairment

The recommended dose of abacavir tablets in patients with mild hepatic impairment (Child-Pugh score 5 to 6) is 200 mg twice daily. To enable dose reduction, abacavir oral solution (10 mL twice daily) should be used for the treatment of these patients. The safety, efficacy, and pharmacokinetic properties of abacavir have not been established in patients with moderate to severe hepatic impairment; therefore, abacavir tablets are contraindicated in these patients.

3 DOSAGE FORMS AND STRENGTHS

Abacavir Tablets, USP are available containing abacavir sulfate, USP equivalent to 300 mg of abacavir.

The 300 mg tablets are peach film-coated, capsule shaped, scored tablets debossed with M on one side of the score and 120 on the other side of the score on one side of the tablet and blank on the other side.

4 CONTRAINDICATIONS

Abacavir tablets are contraindicated in patients with:

- previously demonstrated hypersensitivity to abacavir or any other component of the products. NEVER restart abacavir tablets or any other abacavir-containing product following a hypersensitivity reaction to abacavir, regardless of HLA-B*5701 status [see Warnings and Precautions (5.1), Adverse Reactions (6)].
- moderate or severe hepatic impairment [see Dosage and Administration (2.3)].

5 WARNINGS AND PRECAUTIONS

5.1 Hypersensitivity Reaction

Serious and sometimes fatal hypersensitivity reactions have been associated with abacavir tablets and other abacavir-containing products. Patients who carry the HLA-B*5701 allele are at high risk for experiencing a hypersensitivity reaction to abacavir. Prior to initiating therapy with abacavir, screening for the HLA-B*5701 allele is recommended; this approach has been found to decrease the risk of a hypersensitivity reaction. Screening is also recommended prior to reinitiation of abacavir in patients of unknown HLA-B*5701 status who have previously tolerated abacavir. For HLA-B*5701-positive patients, treatment with an abacavir-containing regimen is not recommended and should be considered only with close medical supervision and under exceptional circumstances when the potential benefit outweighs the risk.

HLA-B*5701-negative patients may develop a hypersensitivity reaction to abacavir; however, this occurs significantly less frequently than in HLA-B*5701-positive patients. Regardless of HLA-B*5701 status, permanently discontinue abacavir if hypersensitivity cannot be ruled out, even when other diagnoses are possible.

Important information on signs and symptoms of hypersensitivity, as well as clinical management, is presented below.

Signs and Symptoms of Hypersensitivity

Hypersensitivity to abacavir is a multi-organ clinical syndrome usually characterized by a sign or symptom in two or more of the following groups.

Group 1: Fever

Group 2: Rash

Group 3: Gastrointestinal (including nausea, vomiting, diarrhea, or abdominal pain)

Group 4: Constitutional (including generalized malaise, fatigue, or achiness)

Group 5: Respiratory (including dyspnea, cough, or pharyngitis).

Hypersensitivity to abacavir following the presentation of a single sign or symptom has been reported infrequently.

Hypersensitivity to abacavir was reported in approximately 8% of 2,670 subjects (n = 206) in nine clinical trials (range: 2% to 9%) with enrollment from November 1999 to February 2002. Data on time to onset and symptoms of suspected hypersensitivity were collected on a detailed data collection module. The frequencies of symptoms are shown in Figure 1. Symptoms usually appeared within the first 6 weeks of treatment with abacavir, although the reaction may occur at any time during therapy. Median time to onset was 9 days; 89% appeared within the first 6 weeks; 95% of subjects reported symptoms from two or more of the five groups listed above.

Figure 1. Hypersensitivity-related Symptoms Reported with ≥ 10% Frequency in Clinical Trials (n = 206 Subjects)

Other less common signs and symptoms of hypersensitivity include lethargy, myolysis, edema, abnormal chest x-ray findings (predominantly infiltrates, which can be localized), and paresthesia. Anaphylaxis, liver failure, renal failure, hypotension, adult respiratory distress syndrome, respiratory failure, and death have occurred in association with hypersensitivity reactions. In one trial, four subjects (11%) receiving abacavir 600 mg once daily experienced hypotension with a hypersensitivity reaction compared with zero subjects receiving abacavir 300 mg twice daily.

Physical findings associated with hypersensitivity to abacavir in some patients include lymphadenopathy, mucous membrane lesions (conjunctivitis and mouth ulcerations), and rash. The rash usually appears maculopapular or urticarial, but may be variable in appearance. There have been reports of erythema multiforme. Hypersensitivity reactions have occurred without rash.

Laboratory abnormalities associated with hypersensitivity to abacavir in some patients include elevated liver function tests, elevated creatine phosphokinase, elevated creatinine, and lymphopenia.

Clinical Management of Hypersensitivity

Discontinue abacavir as soon as a hypersensitivity reaction is suspected. To minimize the risk of a life threatening hypersensitivity reaction, permanently discontinue abacavir if hypersensitivity cannot be ruled out, even when other diagnoses are possible (e.g., acute onset respiratory diseases such as pneumonia, bronchitis, pharyngitis, or influenza; gastroenteritis; or reactions to other medications).

Following a hypersensitivity reaction to abacavir, NEVER restart abacavir tablets or any other abacavir-containing product because more severe symptoms can occur within hours and may include life threatening hypotension and death.

When therapy with abacavir has been discontinued for reasons other than symptoms of a hypersensitivity reaction, and if reinitiation of abacavir tablets or any other abacavir-containing product is under consideration, carefully evaluate the reason for discontinuation of abacavir to ensure that the patient did not have symptoms of a hypersensitivity reaction. If the patient is of unknown HLA-B*5701 status, screening for the allele is recommended prior to reinitiation of abacavir.

If hypersensitivity cannot be ruled out, DO NOT reintroduce abacavir tablets or any other abacavir-containing product. Even in the absence of the HLA-B*5701 allele, it is important to permanently discontinue abacavir and not rechallenge with abacavir if a hypersensitivity reaction cannot be ruled out on clinical grounds, due to the potential for a severe or even fatal reaction.

If symptoms consistent with hypersensitivity are not identified, reintroduction can be undertaken with continued monitoring for symptoms of a hypersensitivity reaction. Make patients aware that a hypersensitivity reaction can occur with reintroduction of abacavir tablets or any other abacavir-containing product and that reintroduction of abacavir tablets or any other abacavir-containing product needs to be undertaken only if medical care can be readily accessed by the patient or others.

Risk Factor: HLA-B*5701 Allele: Trials have shown that carriage of the HLA-B*5701 allele is associated with a significantly increased risk of a hypersensitivity reaction to abacavir.

CNA106030 (PREDICT-1), a randomized, double-blind trial, evaluated the clinical utility of prospective HLA-B*5701 screening on the incidence of abacavir hypersensitivity reaction in abacavir-naive HIV-1-infected adults (n = 1,650). In this trial, use of pre-therapy screening for the HLA-B*5701 allele and exclusion of subjects with this allele reduced the incidence of clinically suspected abacavir hypersensitivity reactions from 7.8% (66/847) to 3.4% (27/803). Based on this trial, it is estimated that 61% of patients with the HLA-B*5701 allele will develop a clinically suspected hypersensitivity reaction during the course of abacavir treatment compared with 4% of patients who do not have the HLA-B*5701 allele.

Screening for carriage of the HLA-B*5701 allele is recommended prior to initiating treatment with abacavir. Screening is also recommended prior to reinitiation of abacavir in patients of unknown HLA-B*5701 status who have previously tolerated abacavir. For HLA-B*5701-positive patients, initiating or reinitiating treatment with an abacavir-containing regimen is not recommended and should be considered only with close medical supervision and under exceptional circumstances where potential benefit outweighs the risk.

Skin patch testing is used as a research tool and should not be used to aid in the clinical diagnosis of abacavir hypersensitivity.

In any patient treated with abacavir, the clinical diagnosis of hypersensitivity reaction must remain the basis of clinical decision-making. Even in the absence of the HLA-B*5701 allele, it is important to permanently discontinue abacavir and not rechallenge with abacavir if a hypersensitivity reaction cannot be ruled out on clinical grounds, due to the potential for a severe or even fatal reaction.

5.2 Lactic Acidosis/Severe Hepatomegaly with Steatosis

Lactic acidosis and severe hepatomegaly with steatosis, including fatal cases, have been reported with the use of nucleoside analogues alone or in combination, including abacavir and other antiretrovirals. A majority of these cases have been in women. Obesity and prolonged nucleoside exposure may be risk factors. Particular caution should be exercised when administering abacavir to any patient with known risk factors for liver disease; however, cases have also been reported in patients with no known risk factors. Treatment with abacavir should be suspended in any patient who develops clinical or laboratory findings suggestive of lactic acidosis or pronounced hepatotoxicity (which may include hepatomegaly and steatosis even in the absence of marked transaminase elevations).

5.3 Immune Reconstitution Syndrome

Immune reconstitution syndrome has been reported in patients treated with combination antiretroviral therapy, including abacavir. During the initial phase of combination antiretroviral treatment, patients whose immune systems respond may develop an inflammatory response to indolent or residual opportunistic infections (such as Mycobacterium avium infection, cytomegalovirus, Pneumocystis jirovecii pneumonia [PCP], or tuberculosis), which may necessitate further evaluation and treatment.

Autoimmune disorders (such as Graves’ disease, polymyositis, and Guillain-Barré syndrome) have also been reported to occur in the setting of immune reconstitution, however, the time to onset is more variable, and can occur many months after initiation of treatment.

5.4 Fat Redistribution

Redistribution/accumulation of body fat including central obesity, dorsocervical fat enlargement (buffalo hump), peripheral wasting, facial wasting, breast enlargement, and “cushingoid appearance” have been observed in patients receiving antiretroviral therapy. The mechanism and long-term consequences of these events are currently unknown. A causal relationship has not been established.

5.5 Myocardial Infarction

In a published prospective, observational, epidemiological study designed to investigate the rate of myocardial infarction in patients on combination antiretroviral therapy, the use of abacavir within the previous 6 months was correlated with an increased risk of myocardial infarction (MI).^1 In a sponsor-conducted pooled analysis of clinical trials, no excess risk of myocardial infarction was observed in abacavir-treated subjects as compared with control subjects. In totality, the available data from the observational cohort and from clinical trials are inconclusive.

As a precaution, the underlying risk of coronary heart disease should be considered when prescribing antiretroviral therapies, including abacavir, and action taken to minimize all modifiable risk factors (e.g., hypertension, hyperlipidemia, diabetes mellitus, smoking).

6 ADVERSE REACTIONS

The following adverse reactions are discussed in greater detail in other sections of the labeling:

- Serious and sometimes fatal hypersensitivity reaction. In one trial, once daily dosing of abacavir was associated with more severe hypersensitivity reactions [see Boxed Warning, Warnings and Precautions (5.1)].
- Lactic acidosis and severe hepatomegaly [see Boxed Warning, Warnings and Precautions (5.2)].
- Immune reconstitution syndrome [see Warnings and Precautions (5.3)].
- Fat redistribution [see Warnings and Precautions (5.4)].
- Myocardial infarction [see Warnings and Precautions (5.5)].

6.1 Clinical Trials Experience

Because clinical trials are conducted under widely varying conditions, adverse reaction rates observed in the clinical trials of a drug cannot be directly compared with rates in the clinical trials of another drug and may not reflect the rates observed in practice.

Therapy-naive Adults

Treatment-emergent clinical adverse reactions (rated by the investigator as moderate or severe) with a greater than or equal to 5% frequency during therapy with abacavir 300 mg twice daily, lamivudine 150 mg twice daily, and efavirenz 600 mg daily compared with zidovudine 300 mg twice daily, lamivudine 150 mg twice daily, and efavirenz 600 mg daily from CNA30024 are listed in Table 2.

Table 2. Treatment-emergent (All Causality) Adverse Reactions of at Least Moderate Intensity (Grades 2 to 4, ≥ 5% Frequency) in Therapy-naive Adults (CNA30024 [This trial used double-blind ascertainment of suspected hypersensitivity reactions. During the blinded portion of the trial, suspected hypersensitivity to abacavir was reported by investigators in 9% of 324 subjects in the abacavir group and 3% of 325 subjects in the zidovudine group.]) Through 48 Weeks of Treatment
Adverse Reaction | Abacavir plus Lamivudine plus Efavirenz (n = 324) | Zidovudine plus Lamivudine plus Efavirenz (n = 325)
Dreams/sleep disorders | 10% | 10%
Drug hypersensitivity | 9% | < 1% [Ten (3%) cases of suspected drug hypersensitivity were reclassified as not being due to abacavir following unblinding.]
Headaches/migraine | 7% | 11%
Nausea | 7% | 11%
Fatigue/malaise | 7% | 10%
Diarrhea | 7% | 6%
Rashes | 6% | 12%
Abdominal pain/gastritis/gastrointestinal signs and symptoms | 6% | 8%
Depressive disorders | 6% | 6%
Dizziness | 6% | 6%
Musculoskeletal pain | 6% | 5%
Bronchitis | 4% | 5%
Vomiting | 2% | 9%

Treatment-emergent clinical adverse reactions (rated by the investigator as moderate or severe) with a greater than or equal to 5% frequency during therapy with abacavir 300 mg twice daily, lamivudine 150 mg twice daily, and zidovudine 300 mg twice daily compared with indinavir 800 mg 3 times daily, lamivudine 150 mg twice daily, and zidovudine 300 mg twice daily from CNA3005 are listed in Table 3.

Table 3. Treatment-emergent (All Causality) Adverse Reactions of at Least Moderate Intensity (Grades 2 to 4, ≥ 5% Frequency) in Therapy-naive Adults (CNA3005) Through 48 Weeks of Treatment
Adverse Reaction | Abacavir plus Lamivudine/Zidovudine (n = 262) | Indinavir plus Lamivudine/Zidovudine (n = 264)
Nausea | 19% | 17%
Headache | 13% | 9%
Malaise and fatigue | 12% | 12%
Nausea and vomiting | 10% | 10%
Hypersensitivity reaction | 8% | 2%
Diarrhea | 7% | 5%
Fever and/or chills | 6% | 3%
Depressive disorders | 6% | 4%
Musculoskeletal pain | 5% | 7%
Skin rashes | 5% | 4%
Ear/nose/throat infections | 5% | 4%
Viral respiratory infections | 5% | 5%
Anxiety | 5% | 3%
Renal signs/symptoms | < 1% | 5%
Pain (non-site-specific) | < 1% | 5%

Five subjects receiving abacavir in CNA3005 experienced worsening of preexisting depression compared with none in the indinavir arm. The background rates of preexisting depression were similar in the two treatment arms.

Abacavir Once Daily Versus Abacavir Twice Daily (CNA30021)

Treatment-emergent clinical adverse reactions (rated by the investigator as at least moderate) with a greater than or equal to 5% frequency during therapy with abacavir 600 mg once daily or abacavir 300 mg twice daily both in combination with lamivudine 300 mg once daily and efavirenz 600 mg once daily from CNA30021 were similar. For hypersensitivity reactions, subjects receiving abacavir once daily showed a rate of 9% in comparison with a rate of 7% for subjects receiving abacavir twice daily. However, subjects receiving abacavir 600 mg once daily, experienced a significantly higher incidence of severe drug hypersensitivity reactions and severe diarrhea compared with subjects who received abacavir 300 mg twice daily. Five percent (5%) of subjects receiving abacavir 600 mg once daily had severe drug hypersensitivity reactions compared with 2% of subjects receiving abacavir 300 mg twice daily. Two percent (2%) of subjects receiving abacavir 600 mg once daily had severe diarrhea while none of the subjects receiving abacavir 300 mg twice daily had this event.

Laboratory Abnormalities

Laboratory abnormalities (Grades 3 to 4) in therapy-naive adults during therapy with abacavir 300 mg twice daily, lamivudine 150 mg twice daily, and efavirenz 600 mg daily compared with zidovudine 300 mg twice daily, lamivudine 150 mg twice daily, and efavirenz 600 mg daily from CNA30024 are listed in Table 4.

Table 4. Laboratory Abnormalities (Grades 3 to 4) in Therapy-naive Adults (CNA30024) Through 48 Weeks of Treatment
Grade 3/4 Laboratory Abnormalities | Abacavir plus Lamivudine plus Efavirenz (n = 324) | Zidovudine plus Lamivudine plus Efavirenz (n = 325)
Elevated CPK (> 4 x ULN) | 8% | 8%
Elevated ALT (> 5 x ULN) | 6% | 6%
Elevated AST (> 5 x ULN) | 6% | 5%
Hypertriglyceridemia (> 750 mg/dL) | 6% | 5%
Hyperamylasemia (> 2 x ULN) | 4% | 5%
Neutropenia (ANC < 750/mm^3) | 2% | 4%
Anemia (Hgb ≤ 6.9 gm/dL) | < 1% | 2%
Thrombocytopenia (Platelets < 50,000/mm^3) | 1% | < 1%
Leukopenia (WBC ≤ 1,500/mm^3) | < 1% | 2%
ULN = Upper limit of normal.
n = Number of subjects assessed.

Laboratory abnormalities in CNA3005 are listed in Table 5.

Table 5. Treatment-emergent Laboratory Abnormalities (Grades 3 to 4) in CNA3005
Grade 3/4 Laboratory Abnormalities | Number of Subjects by Treatment Group
Grade 3/4 Laboratory Abnormalities | Abacavir plus Lamivudine/Zidovudine (n = 262) | Indinavir plus Lamivudine/Zidovudine (n = 264)
Elevated CPK (> 4 x ULN) | 18 (7%) | 18 (7%)
ALT (> 5 x ULN) | 16 (6%) | 16 (6%)
Neutropenia (< 750/mm^3) | 13 (5%) | 13 (5%)
Hypertriglyceridemia (> 750 mg/dL) | 5 (2%) | 3 (1%)
Hyperamylasemia (> 2 x ULN) | 5 (2%) | 1 (< 1%)
Hyperglycemia (> 13.9 mmol/L) | 2 (< 1%) | 2 (< 1%)
Anemia (Hgb ≤ 6.9 g/dL) | 0 (0%) | 3 (1%)
ULN = Upper limit of normal. n = Number of subjects assessed.

The frequencies of treatment-emergent laboratory abnormalities were comparable between treatment groups in CNA30021.

Therapy-experienced Pediatric Subjects

Treatment-emergent clinical adverse reactions (rated by the investigator as moderate or severe) with a greater than or equal to 5% frequency during therapy with abacavir 8 mg/kg twice daily, lamivudine 4 mg/kg twice daily and zidovudine 180 mg/m^2 twice daily compared with lamivudine 4 mg/kg twice daily and zidovudine 180 mg/m^2 twice daily from CNA3006 are listed in Table 6.

Table 6. Treatment-emergent (All Causality) Adverse Reactions of at Least Moderate Intensity (Grades 2 to 4, ≥ 5% Frequency) in Therapy-experienced Pediatric Subjects (CNA3006) Through 16 Weeks of Treatment
Adverse Reaction | Abacavir plus Lamivudine plus Zidovudine (n = 102) | Lamivudine plus Zidovudine (n = 103)
Fever and/or chills | 9% | 7%
Nausea and vomiting | 9% | 2%
Skin rashes | 7% | 1%
Ear/nose/throat infections | 5% | 1%
Pneumonia | 4% | 5%
Headache | 1% | 5%

Laboratory Abnormalities

In CNA3006, laboratory abnormalities (anemia, neutropenia, liver function test abnormalities, and CPK elevations) were observed with similar frequencies as in a trial of therapy-naive adults (CNA30024). Mild elevations of blood glucose were more frequent in pediatric patients receiving abacavir (CNA3006) as compared with adult subjects (CNA30024).

Other Adverse Events

In addition to adverse reactions and laboratory abnormalities reported in Tables 2, 3, 4, 5, and 6, other adverse reactions observed in the expanded access program were pancreatitis and increased GGT.

6.2 Post-marketing Experience

In addition to adverse reactions reported from clinical trials, the following reactions have been identified during post-marketing use of abacavir. Because they are reported voluntarily from a population of unknown size, estimates of frequency cannot be made. These reactions have been chosen for inclusion due to a combination of their seriousness, frequency of reporting, or potential causal connection to abacavir.

Body as a Whole: Redistribution/accumulation of body fat.

Cardiovascular: Myocardial infarction.

Hepatic: Lactic acidosis and hepatic steatosis.

Skin: Suspected Stevens-Johnson syndrome (SJS) and toxic epidermal necrolysis (TEN) have been reported in patients receiving abacavir primarily in combination with medications known to be associated with SJS and TEN, respectively. Because of the overlap of clinical signs and symptoms between hypersensitivity to abacavir and SJS and TEN, and the possibility of multiple drug sensitivities in some patients, abacavir should be discontinued and not restarted in such cases.

There have also been reports of erythema multiforme with abacavir use.

7 DRUG INTERACTIONS

7.1 Ethanol

Abacavir has no effect on the pharmacokinetic properties of ethanol. Ethanol decreases the elimination of abacavir causing an increase in overall exposure [see Clinical Pharmacology (12.3)].

7.2 Methadone

The addition of methadone has no clinically significant effect on the pharmacokinetic properties of abacavir. In a trial of 11 HIV-1-infected subjects receiving methadone-maintenance therapy with 600 mg of abacavir twice daily (twice the currently recommended dose), oral methadone clearance increased [see Clinical Pharmacology (12.3)]. This alteration will not result in a methadone dose modification in the majority of patients; however, an increased methadone dose may be required in a small number of patients.

8 USE IN SPECIFIC POPULATIONS

Teratogenic Effects: Pregnancy Category C

Studies in pregnant rats showed that abacavir is transferred to the fetus through the placenta. Fetal malformations (increased incidences of fetal anasarca and skeletal malformations) and developmental toxicity (depressed fetal body weight and reduced crown-rump length) were observed in rats at a dose which produced 35 times the human exposure based on AUC. Embryonic and fetal toxicities (increased resorptions, decreased fetal body weights) and toxicities to the offspring (increased incidence of stillbirth and lower body weights) occurred at half of the above-mentioned dose in separate fertility studies conducted in rats. In the rabbit, no developmental toxicity and no increases in fetal malformations occurred at doses that produced 8.5 times the human exposure at the recommended dose based on AUC.

There are no adequate and well controlled studies in pregnant women. Abacavir should be used during pregnancy only if the potential benefits outweigh the risk.

Antiretroviral Pregnancy Registry

To monitor maternal-fetal outcomes of pregnant women exposed to abacavir, an Antiretroviral Pregnancy Registry has been established. Physicians are encouraged to register patients by calling 1-800-258-4263.

8.3 Nursing Mothers

The Centers for Disease Control and Prevention recommend that HIV-1-infected mothers not breast-feed their infants to avoid risking postnatal transmission of HIV-1 infection.

Although it is not known if abacavir is excreted in human milk, abacavir is secreted into the milk of lactating rats. Because of both the potential for HIV-1 transmission and the potential for serious adverse reactions in nursing infants, mothers should be instructed not to breast-feed if they are receiving abacavir.

8.4 Pediatric Use

The safety and effectiveness of abacavir have been established in pediatric patients 3 months to 13 years of age. Use of abacavir in these age groups is supported by pharmacokinetic trials and evidence from adequate and well controlled trials of abacavir in adults and pediatric patients [see Dosage and Administration (2.2), Clinical Pharmacology (12.3), Clinical Studies (14.2)].

8.5 Geriatric Use

Clinical studies of abacavir did not include sufficient numbers of patients aged 65 and over to determine whether they respond differently from younger patients. In general, dose selection for an elderly patient should be cautious, reflecting the greater frequency of decreased hepatic, renal, or cardiac function, and of concomitant disease or other drug therapy.

10 OVERDOSAGE

There is no known antidote for abacavir. It is not known whether abacavir can be removed by peritoneal dialysis or hemodialysis.

11 DESCRIPTION

Abacavir sulfate is a synthetic carbocyclic nucleoside analogue with inhibitory activity against HIV-1. The chemical name of abacavir sulfate is (1S,cis)-4-[2-amino-6-(cyclopropylamino)-9H-purin-9-yl]-2-cyclopentene-1-methanol sulfate (salt) (2:1). Abacavir sulfate is the enantiomer with 1S, 4R absolute configuration on the cyclopentene ring. It has a molecular formula of (C14H18N6O)2•H2SO4 and a molecular weight of 670.76 daltons. It has the following structural formula:

Abacavir sulfate, USP is an off-white to cream colored crystalline powder with a solubility of approximately 77 mg/mL in distilled water at 25°C. It has an octanol/water (pH 7.1 to 7.3) partition coefficient (log P) of approximately 1.20 at 25°C.

Abacavir tablets, USP are for oral administration. Each tablet contains abacavir sulfate, USP equivalent to 300 mg of abacavir as active ingredient and the following inactive ingredients: colloidal silicon dioxide, hypromellose, magnesium stearate, microcrystalline cellulose, polyethylene glycol, red iron oxide, sodium starch glycolate, titanium dioxide and yellow iron oxide.

In vivo, abacavir sulfate dissociates to its free base, abacavir. All dosages for abacavir tablets are expressed in terms of abacavir.

12 CLINICAL PHARMACOLOGY

12.1 Mechanism of Action

Abacavir is an antiviral agent [see Clinical Pharmacology (12.4)].

Pharmacokinetics in Adults

The pharmacokinetic properties of abacavir have been studied in asymptomatic, HIV-1-infected adult patients after administration of a single intravenous (IV) dose of 150 mg and after single and multiple oral doses. The pharmacokinetic properties of abacavir were independent of dose over the range of 300 to 1,200 mg/day.

Absorption and Bioavailability

Abacavir was rapidly and extensively absorbed after oral administration. The geometric mean absolute bioavailability of the tablet was 83%. After oral administration of 300 mg twice daily in 20 subjects, the steady-state peak serum abacavir concentration (Cmax) was 3 ± 0.89 mcg/mL (mean ± SD) and AUC(0-12 hr) was 6.02 ± 1.73 mcg•hr/mL. After oral administration of a single dose of 600 mg of abacavir in 20 subjects, Cmax was 4.26 ± 1.19 mcg/mL (mean ± SD) and AUC∞ was 11.95 ± 2.51 mcg•hr/mL.

Distribution

The apparent volume of distribution after IV administration of abacavir was
0.86 ± 0.15 L/kg, suggesting that abacavir distributes into extravascular space. In three subjects, the CSF AUC(0-6 hr) to plasma abacavir AUC(0-6 hr) ratio ranged from 27% to 33%.

Binding of abacavir to human plasma proteins is approximately 50%. Binding of abacavir to plasma proteins was independent of concentration. Total blood and plasma drug-related radioactivity concentrations are identical, demonstrating that abacavir readily distributes into erythrocytes.

Metabolism

In humans, abacavir is not significantly metabolized by cytochrome P450 enzymes. The primary routes of elimination of abacavir are metabolism by alcohol dehydrogenase (to form the 5′-carboxylic acid) and glucuronyl transferase (to form the 5′-glucuronide). The metabolites do not have antiviral activity. In vitro experiments reveal that abacavir does not inhibit human CYP3A4, CYP2D6, or CYP2C9 activity at clinically relevant concentrations.

Elimination

Elimination of abacavir was quantified in a mass balance trial following administration of a 600 mg dose of ^14C-abacavir: 99% of the radioactivity was recovered, 1.2% was excreted in the urine as abacavir, 30% as the 5′-carboxylic acid metabolite, 36% as the 5′-glucuronide metabolite and 15% as unidentified minor metabolites in the urine. Fecal elimination accounted for 16% of the dose.

In single-dose trials, the observed elimination half-life (t1/2) was 1.54 ± 0.63 hours. After intravenous administration, total clearance was 0.8 ± 0.24 L/hr/kg (mean ± SD).

Effects of Food on Oral Absorption

Bioavailability of abacavir tablets was assessed in the fasting and fed states. There was no significant difference in systemic exposure (AUC∞) in the fed and fasting states; therefore, abacavir tablets may be administered with or without food. Systemic exposure to abacavir was comparable after administration of abacavir oral solution and abacavir tablets. Therefore, these products may be used interchangeably.

Renal Impairment

The pharmacokinetic properties of abacavir have not been determined in patients with impaired renal function. Renal excretion of unchanged abacavir is a minor route of elimination in humans.

Hepatic Impairment

The pharmacokinetics of abacavir have been studied in subjects with mild hepatic impairment (Child-Pugh score 5 to 6). Results showed that there was a mean increase of 89% in the abacavir AUC, and an increase of 58% in the half-life of abacavir after a single dose of 600 mg of abacavir. The AUCs of the metabolites were not modified by mild liver disease; however, the rates of formation and elimination of the metabolites were decreased. A dose of 200 mg (provided by 10 mL of abacavir oral solution) administered twice daily is recommended for patients with mild liver disease. The safety, efficacy, and pharmacokinetics of abacavir have not been studied in patients with moderate or severe hepatic impairment, therefore abacavir is contraindicated in these patients.

Pediatric Patients

The pharmacokinetics of abacavir have been studied after either single or repeat doses of abacavir in 68 pediatric subjects. Following multiple dose administration of abacavir 8 mg/kg twice daily, steady-state AUC(0-12 hr) and Cmax were 9.8 ± 4.56 mcg•hr/mL and 3.71 ± 1.36 mcg/mL (mean ± SD), respectively [see Use in Specific Populations (8.4)]. In addition, to support dosing of abacavir scored tablet (300 mg) for pediatric patients 14 kg to greater than 30 kg, analysis of actual and simulated pharmacokinetic data indicated comparable exposures are expected following administration of 300 mg scored tablet and the 8 mg/kg dosing regimen using oral solution.

Geriatric Patients

The pharmacokinetics of abacavir have not been studied in patients over 65 years of age.

Gender

A population pharmacokinetic analysis in HIV-1-infected male (n = 304) and female (n = 67) subjects showed no gender differences in abacavir AUC normalized for lean body weight.

Race

There are no significant differences between blacks and Caucasians in abacavir pharmacokinetics.

Drug Interactions

In human liver microsomes, abacavir did not inhibit cytochrome P450 isoforms (2C9, 2D6, 3A4). Based on these data, it is unlikely that clinically significant drug interactions will occur between abacavir and drugs metabolized through these pathways.

Lamivudine and/or Zidovudine

Due to the common metabolic pathways of abacavir and zidovudine via glucuronyl transferase, 15 HIV-1-infected subjects were enrolled in a crossover trial evaluating single doses of abacavir (600 mg), lamivudine (150 mg), and zidovudine (300 mg) alone or in combination. Analysis showed no clinically relevant changes in the pharmacokinetics of abacavir with the addition of lamivudine or zidovudine or the combination of lamivudine and zidovudine. Lamivudine exposure (AUC decreased 15%) and zidovudine exposure (AUC increased 10%) did not show clinically relevant changes with concurrent abacavir.

Ethanol

Due to the common metabolic pathways of abacavir and ethanol via alcohol dehydrogenase, the pharmacokinetic interaction between abacavir and ethanol was studied in 24 HIV-1-infected male subjects. Each subject received the following treatments on separate occasions: a single 600 mg dose of abacavir, 0.7 g/kg ethanol (equivalent to five alcoholic drinks), and abacavir 600 mg plus 0.7 g/kg ethanol. Coadministration of ethanol and abacavir resulted in a 41% increase in abacavir AUC∞ and a 26% increase in abacavir t1/2. In males, abacavir had no effect on the pharmacokinetic properties of ethanol, so no clinically significant interaction is expected in men. This interaction has not been studied in females.

Methadone

In a study of 11 HIV-1-infected subjects receiving methadone-maintenance therapy (40 mg and 90 mg daily), with 600 mg of abacavir twice daily (twice the currently recommended dose), oral methadone clearance increased 22% (90% CI: 6% to 42%). This alteration will not result in a methadone dose modification in the majority of patients; however, an increased methadone dose may be required in a small number of patients. The addition of methadone had no clinically significant effect on the pharmacokinetic properties of abacavir.

12.4 Microbiology

Abacavir is a carbocyclic synthetic nucleoside analogue. Abacavir is converted by cellular enzymes to the active metabolite, carbovir triphosphate (CBV-TP), an analogue of deoxyguanosine-5′-triphosphate (dGTP). CBV-TP inhibits the activity of HIV-1 reverse transcriptase (RT) both by competing with the natural substrate dGTP and by its incorporation into viral DNA. The lack of a 3′-OH group in the incorporated nucleotide analogue prevents the formation of the 5′ to 3′ phosphodiester linkage essential for DNA chain elongation, and therefore, the viral DNA growth is terminated. CBV-TP is a weak inhibitor of cellular DNA polymerases α, β, and γ.

Antiviral Activity

The antiviral activity of abacavir against HIV-1 was evaluated against a T-cell tropic laboratory strain HIV-1IIIB in lymphoblastic cell lines, a monocyte/macrophage tropic laboratory strain HIV-1BaL in primary monocytes/macrophages, and clinical isolates in peripheral blood mononuclear cells. The concentration of drug necessary to effect viral replication by 50 percent (EC50) ranged from 3.7 to 5.8 μM (1 μM = 0.28 mcg/mL) and 0.07 to 1 μM against HIV-1IIIB and HIV-1BaL, respectively, and was 0.26 ± 0.18 μM against eight clinical isolates. The EC50 values of abacavir against different HIV-1 clades (A-G) ranged from 0.0015 to 1.05 μM, and against HIV-2 isolates, from 0.024 to 0.49 μM. Abacavir had synergistic activity in cell culture in combination with the nucleoside reverse transcriptase inhibitor (NRTI) zidovudine, the non-nucleoside reverse transcriptase inhibitor (NNRTI) nevirapine, and the protease inhibitor (PI) amprenavir; and additive activity in combination with the NRTIs didanosine, emtricitabine, lamivudine, stavudine, tenofovir, and zalcitabine. Ribavirin (50 μM) had no effect on the anti–HIV-1 activity of abacavir in cell culture.

Resistance

HIV-1 isolates with reduced susceptibility to abacavir have been selected in cell culture and were also obtained from subjects treated with abacavir. Genotypic analysis of isolates selected in cell culture and recovered from abacavir-treated subjects demonstrated that amino acid substitutions K65R, L74V, Y115F, and M184V/I in RT contributed to abacavir resistance. In a trial of therapy-naive adults receiving abacavir 600 mg once daily (n = 384) or 300 mg twice daily (n = 386), in a background regimen of lamivudine 300 mg once daily and efavirenz 600 mg once daily (CNA30021), the incidence of virologic failure at 48 weeks was similar between the two groups (11% in both arms). Genotypic (n = 38) and phenotypic analyses (n = 35) of virologic failure isolates from this trial showed that the RT substitutions that emerged during abacavir once daily and twice daily therapy were K65R, L74V, Y115F, and M184V/I. The substitution M184V/I was the most commonly observed substitution in virologic failure isolates from subjects receiving abacavir once daily (56%, 10/18) and twice daily (40%, 8/20).

Thirty-nine percent (7/18) of the isolates from subjects who experienced virologic failure in the abacavir once daily arm had a greater than 2.5-fold decrease in abacavir susceptibility with a median-fold decrease of 1.3 (range: 0.5 to 11) compared with 29% (5/17) of the failure isolates in the twice daily arm with a median-fold decrease of 0.92 (range: 0.7 to 13).

Cross-resistance

Cross-resistance has been observed among NRTIs. Isolates containing abacavir resistance-associated substitutions, namely, K65R, L74V, Y115F, and M184V, exhibited cross-resistance to didanosine, emtricitabine, lamivudine, tenofovir, and zalcitabine in cell culture and in subjects. The K65R substitution can confer resistance to abacavir, didanosine, emtricitabine, lamivudine, stavudine, tenofovir, and zalcitabine; the L74V substitution can confer resistance to abacavir, didanosine, and zalcitabine; and the M184V substitution can confer resistance to abacavir, didanosine, emtricitabine, lamivudine, and zalcitabine. An increasing number of thymidine analogue mutations (TAMs: M41L, D67N, K70R, L210W, T215Y/F, K219E/R/H/Q/N) is associated with a progressive reduction in abacavir susceptibility.

13 NONCLINICAL TOXICOLOGY

Carcinogenicity:

Abacavir was administered orally at three dosage levels to separate groups of mice and rats in 2-year carcinogenicity studies. Results showed an increase in the incidence of malignant and non-malignant tumors. Malignant tumors occurred in the preputial gland of males and the clitoral gland of females of both species, and in the liver of female rats. In addition, non-malignant tumors also occurred in the liver and thyroid gland of female rats. These observations were made at systemic exposures in the range of 6 to 32 times the human exposure at the recommended dose. It is not known how predictive the results of rodent carcinogenicity studies may be for humans.

Mutagenicity:

Abacavir induced chromosomal aberrations both in the presence and absence of metabolic activation in an in vitro cytogenetic study in human lymphocytes. Abacavir was mutagenic in the absence of metabolic activation, although it was not mutagenic in the presence of metabolic activation in an L5178Y mouse lymphoma assay. Abacavir was clastogenic in males and not clastogenic in females in an in vivo mouse bone marrow micronucleus assay.

Abacavir was not mutagenic in bacterial mutagenicity assays in the presence and absence of metabolic activation.

Impairment of Fertility:

Abacavir had no adverse effects on the mating performance or fertility of male and female rats at a dose approximately 8 times the human exposure at the recommended dose based on body surface area comparisons.

13.2 Animal Toxicology and/or Pharmacology

Myocardial degeneration was found in mice and rats following administration of abacavir for
2 years. The systemic exposures were equivalent to 7 to 24 times the expected systemic exposure in humans. The clinical relevance of this finding has not been determined.

14 CLINICAL STUDIES

Therapy-naive Adults

CNA30024 was a multicenter, double-blind, controlled trial in which 649 HIV-1-infected, therapy-naive adults were randomized and received either abacavir (300 mg twice daily), lamivudine (150 mg twice daily), and efavirenz (600 mg once daily); or zidovudine (300 mg twice daily), lamivudine (150 mg twice daily), and efavirenz (600 mg once daily). The duration of double-blind treatment was at least 48 weeks. Trial participants were male (81%), Caucasian (51%), black (21%), and Hispanic (26%). The median age was 35 years; the median pretreatment CD4+ cell count was 264 cells/mm^3, and median plasma HIV-1 RNA was 4.79 log10 copies/mL. The outcomes of randomized treatment are provided in Table 7.

Table 7. Outcomes of Randomized Treatment Through Week 48 (CNA30024)
Outcome | Abacavir plus Lamivudine plus Efavirenz (n = 324) | Zidovudine plus Lamivudine plus Efavirenz (n = 325)
Responder [Subjects achieved and maintained confirmed HIV-1 RNA ≤ 50 copies/mL (< 400 copies/mL) through Week 48 (Roche AMPLICOR Ultrasensitive HIV-1 MONITOR®** standard test 1.0 PCR).] | 69% (73%) | 69% (71%)
Virologic failures [Includes viral rebound, insufficient viral response according to the investigator, and failure to achieve confirmed ≤ 50 copies/mL by Week 48.] | 6% | 4%
Discontinued due to adverse reactions | 14% | 16%
Discontinued due to other reasons [Includes consent withdrawn, lost to follow up, protocol violations, those with missing data, clinical progression, and other.] | 10% | 11%

After 48 weeks of therapy, the median CD4+ cell count increases from baseline were 209 cells/mm^3 in the group receiving abacavir and 155 cells/mm^3 in the zidovudine group. Through Week 48, eight subjects (2%) in the group receiving abacavir (five CDC classification C events and three deaths) and five subjects (2%) on the zidovudine arm (three CDC classification C events and two deaths) experienced clinical disease progression.

CNA3005 was a multicenter, double-blind, controlled trial in which 562 HIV-1-infected, therapy-naive adults were randomized to receive either abacavir (300 mg twice daily) plus COMBIVIR®** (lamivudine 150 mg/zidovudine 300 mg twice daily), or indinavir (800 mg 3 times a day) plus COMBIVIR®** twice daily. The trial was stratified at randomization by pre-entry plasma HIV-1 RNA 10,000 to 100,000 copies/mL and plasma HIV-1 RNA greater than 100,000 copies/mL. Trial participants were male (87%), Caucasian (73%), black (15%), and Hispanic (9%). At baseline the median age was 36 years; the median baseline CD4+ cell count was 360 cells/mm^3, and median baseline plasma HIV-1 RNA was 4.8 log10 copies/mL. Proportions of subjects with plasma HIV-1 RNA less than 400 copies/mL (using Roche AMPLICOR HIV-1 MONITOR Test) through 48 weeks of treatment are summarized in Table 8.

Table 8. Outcomes of Randomized Treatment Through Week 48 (CNA3005)
Outcome | Abacavir plus Lamivudine/Zidovudine (n = 262) | Indinavir plus Lamivudine/Zidovudine (n = 265)
Responder [Subjects achieved and maintained confirmed HIV-1 RNA < 400 copies/mL.] | 49% | 50%
Virologic failures [Includes viral rebound and failure to achieve confirmed < 400 copies/mL by Week 48.] | 31% | 28%
Discontinued due to adverse reactions | 10% | 12%
Discontinued due to other reasons [Includes consent withdrawn, lost to follow up, protocol violations, those with missing data, clinical progression, and other.] | 11% | 10%

Treatment response by plasma HIV-1 RNA strata is shown in Table 9.

Table 9. Proportions of Responders Through Week 48 By Screening Plasma HIV-1 RNA Levels (CNA3005)
Screening HIV-1 RNA (copies/mL) | Abacavir plus Lamivudine/Zidovudine (n = 262) |  | Indinavir plus Lamivudine/Zidovudine (n = 265)
Screening HIV-1 RNA (copies/mL) | < 400 copies/mL | n | < 400 copies/mL | n
≥ 10,000 to ≤ 100,000 | 50% | 166 | 48% | 165
> 100,000 | 48% | 96 | 52% | 100

In subjects with baseline viral load greater than 100,000 copies/mL, percentages of subjects with HIV-1 RNA levels less than 50 copies/mL were 31% in the group receiving abacavir versus 45% in the group receiving indinavir.

Through Week 48, an overall mean increase in CD4+ cell count of about 150 cells/mm^3 was observed in both treatment arms. Through Week 48, nine subjects (3.4%) in the group receiving abacavir (six CDC classification C events and three deaths) and three subjects (1.5%) in the group receiving indinavir (two CDC classification C events and one death) experienced clinical disease progression.

CNA30021 was an international, multicenter, double-blind, controlled trial in which 770 HIV-1-infected, therapy-naive adults were randomized and received either abacavir 600 mg once daily or abacavir 300 mg twice daily, both in combination with lamivudine 300 mg once daily and efavirenz 600 mg once daily. The double-blind treatment duration was at least 48 weeks. Trial participants had a mean age of 37 years; were male (81%), Caucasian (54%), black (27%), and American Hispanic (15%). The median baseline CD4+ cell count was 262 cells/mm^3 (range: 21 to 918 cells/mm^3) and the median baseline plasma HIV-1 RNA was 4.89 log10 copies/mL (range: 2.6 to 6.99 log10 copies/mL).

The outcomes of randomized treatment are provided in Table 10.

Table 10. Outcomes of Randomized Treatment Through Week 48 (CNA30021)
Outcome | Abacavir 600 mg q.d. plus EPIVIR®** plus Efavirenz (n = 384) | Abacavir 300 mg b.i.d. plus EPIVIR®** plus Efavirenz (n = 386)
Responder [Subjects achieved and maintained confirmed HIV-1 RNA < 50 copies/mL (<400 copies/mL) through Week 48 (Roche AMPLICOR Ultrasensitive HIV-1 MONITOR standard test version 1.0).] | 64% (71%) | 65% (72%)
Virologic failures [Includes viral rebound, failure to achieve confirmed < 50 copies/mL (< 400 copies/mL) by Week 48, and insufficient viral load response.] | 11% (5%) | 11% (5%)
Discontinued due to adverse reactions | 13% | 11%
Discontinued due to other reasons [Includes consent withdrawn, lost to follow up, protocol violations, clinical progression, and other.] | 11% | 13%

After 48 weeks of therapy, the median CD4+ cell count increases from baseline were 188 cells/mm^3 in the group receiving abacavir 600 mg once daily and 200 cells/mm^3 in the group receiving abacavir 300 mg twice daily. Through Week 48, six subjects (2%) in the group receiving abacavir 600 mg once daily (four CDC classification C events and two deaths) and ten subjects (3%) in the group receiving abacavir 300 mg twice daily (seven CDC classification C events and three deaths) experienced clinical disease progression. None of the deaths were attributed to trial medications.

Therapy-experienced Pediatric Subjects

CNA3006 was a randomized, double-blind trial comparing abacavir 8 mg/kg twice daily plus lamivudine 4 mg/kg twice daily plus zidovudine 180 mg/m^2 twice daily versus lamivudine 4 mg/kg twice daily plus zidovudine 180 mg/m^2 twice daily. Two hundred and five therapy-experienced pediatric subjects were enrolled: female (56%), Caucasian (17%), black (50%), Hispanic (30%), median age of 5.4 years, baseline CD4+ cell percent greater than 15% (median = 27%), and median baseline plasma HIV-1 RNA of 4.6 log10 copies/mL. Eighty percent and 55% of subjects had prior therapy with zidovudine and lamivudine, respectively, most often in combination. The median duration of prior nucleoside analogue therapy was 2 years. At 16 weeks the proportion of subjects responding based on plasma HIV-1 RNA less than or equal to 400 copies/mL was significantly higher in subjects receiving abacavir plus lamivudine plus zidovudine compared with subjects receiving lamivudine plus zidovudine, 13% versus 2%, respectively. Median plasma HIV-1 RNA changes from baseline were -0.53 log10 copies/mL in the group receiving abacavir plus lamivudine plus zidovudine compared with -0.21 log10 copies/mL in the group receiving lamivudine plus zidovudine. Median CD4+ cell count increases from baseline were 69 cells/mm^3 in the group receiving abacavir plus lamivudine plus zidovudine and 9 cells/mm^3 in the group receiving lamivudine plus zidovudine.

15 REFERENCES

1. Data Collection on Adverse Events of Anti-HIV Drugs (D:A:D) Study Group. Lancet. 2008;371 (9622):1417-1426.

16 HOW SUPPLIED/STORAGE AND HANDLING

Abacavir Tablets, USP are available containing abacavir sulfate, USP equivalent to 300 mg of abacavir.

The 300 mg tablets are peach film-coated, capsule shaped, scored tablets debossed with M on one side of the score and 120 on the other side of the score on one side of the tablet and blank on the other side.

They are supplied by State of Florida DOH Central Pharmacy as follows:

NDC | Strength | Quantity/Form | Color | Source Prod. Code
53808-0627-1 | 300 mg | 30 Tablets in a Blister Pack | peach | 0378-4105

Store at 20° to 25°C (68° to 77°F). [See USP Controlled Room Temperature.]

Dispense in original container with attached prescribing information that contains the Medication Guide and a Warning Card.

17 PATIENT COUNSELING INFORMATION

See FDA-approved patient labeling (Medication Guide)

17.1 Information About Therapy with Abacavir Tablets

Hypersensitivity Reaction: Inform patients:

- that a Medication Guide and Warning Card summarizing the symptoms of the abacavir hypersensitivity reaction and other product information will be dispensed by the pharmacist with each new prescription and refill of abacavir tablets, and encourage the patient to read the Medication Guide and Warning Card every time to obtain any new information that may be present about abacavir tablets. (The complete text of the Medication Guide is reprinted at the end of this document.)
- to carry the Warning Card with them.
- how to identify a hypersensitivity reaction [see Medication Guide].
- that if they develop symptoms consistent with a hypersensitivity reaction they should call their doctor right away to determine if they should stop taking abacavir tablets.
- that a hypersensitivity reaction can worsen and lead to hospitalization or death if abacavir tablets are not immediately discontinued.
- that in one trial, more severe hypersensitivity reactions were seen when abacavir was dosed 600 mg once daily.
- to not restart abacavir tablets or any other abacavir-containing product following a hypersensitivity reaction because more severe symptoms can occur within hours and may include life threatening hypotension and death.
- that a hypersensitivity reaction is usually reversible if it is detected promptly and abacavir tablets are stopped right away.
- that if they have interrupted abacavir for reasons other than symptoms of hypersensitivity (for example, those who have an interruption in drug supply), a serious or fatal hypersensitivity reaction may occur with reintroduction of abacavir.
- to not restart abacavir tablets or any other abacavir-containing product without medical consultation and that restarting abacavir needs to be undertaken only if medical care can be readily accessed by the patient or others.
- abacavir tablets should not be coadministered with EPZICOM®** (abacavir sulfate and lamivudine) Tablets or TRIZIVIR®** (abacavir sulfate, lamivudine, and zidovudine) Tablets.

Lactic Acidosis/Hepatomegaly: Inform patients that some HIV medicines, including abacavir tablets, can cause a rare, but serious condition called lactic acidosis with liver enlargement (hepatomegaly) [see Boxed Warning, Warnings and Precautions (5.2)].

Redistribution/Accumulation of Body Fat: Inform patients that redistribution or accumulation of body fat may occur in patients receiving antiretroviral therapy and that the cause and long-term health effects of these conditions are not known at this time [see Warnings and Precautions (5.4)].

Information About HIV-1 Infection: Abacavir is not a cure for HIV-1 infection and patients may continue to experience illnesses associated with HIV-1 infection, including opportunistic infections. Patients should remain under the care of a physician when using abacavir tablets.

Patients should be advised to avoid doing things that can spread HIV-1 infection to others.

- Do not share needles or other injection equipment.
- Do not share personal items that can have blood or body fluids on them, like toothbrushes and razor blades.
- Do not have any kind of sex without protection. Always practice safe sex by using a latex or polyurethane condom to lower the chance of sexual contact with semen, vaginal secretions, or blood.
- Do not breast-feed. We do not know if abacavir can be passed to your baby in your breast milk and whether it could harm your baby. Also, mothers with HIV-1 should not breast-feed because HIV-1 can be passed to the baby in the breast milk.

Patients should be informed to take all HIV medications exactly as prescribed.

MEDICATION GUIDE
ABACAVIR TABLETS, USP
(a bak′ a vir sul′ fate)
300 mg

Read this Medication Guide before you start taking abacavir tablets and each time you get a refill. There may be new information. This information does not take the place of talking to your healthcare provider about your medical condition or your treatment. Be sure to carry your Abacavir Tablets Warning Card with you at all times.

What is the most important information I should know about abacavir tablets?

1. Serious allergic reaction (hypersensitivity reaction). Abacavir tablets contain abacavir (also contained in EPZICOM®** and TRIZIVIR®**). Patients taking abacavir tablets may have a serious allergic reaction (hypersensitivity reaction) that can cause death. Your risk of this allergic reaction is much higher if you have a gene variation called HLA-B*5701. Your healthcare provider can determine with a blood test if you have this gene variation.

If you get a symptom from two or more of the following groups while taking abacavir tablets, call your healthcare provider right away to find out if you should stop taking abacavir tablets.

 | Symptom(s)
Group 1 | Fever
Group 2 | Rash
Group 3 | Nausea, vomiting, diarrhea, abdominal (stomach area) pain
Group 4 | Generally ill feeling, extreme tiredness, or achiness
Group 5 | Shortness of breath, cough, sore throat

A list of these symptoms is on the Warning Card your pharmacist gives you. Carry this Warning Card with you at all times.

If you stop abacavir tablets because of an allergic reaction, never take abacavir tablets (abacavir sulfate) or any other abacavir-containing medicine (EPZICOM®** and TRIZIVIR®**) again. If you take abacavir tablets or any other abacavir-containing medicine again after you have had an allergic reaction, within hours you may get life threatening symptoms that may include very low blood pressure or death. If you stop abacavir tablets for any other reason, even for a few days, and you are not allergic to abacavir, talk with your healthcare provider before taking it again. Taking abacavir tablets again can cause a serious allergic or life threatening reaction, even if you never had an allergic reaction to it before.

If your healthcare provider tells you that you can take abacavir again, start taking it when you are around medical help or people who can call a healthcare provider if you need one.

2. Lactic Acidosis (buildup of acid in the blood). Some human immunodeficiency virus (HIV) medicines, including abacavir tablets, can cause a rare but serious condition called lactic acidosis. Lactic acidosis is a serious medical emergency that can cause death and must be treated in the hospital.

Call your healthcare provider right away if you get any of the following signs or symptoms of lactic acidosis:

- you feel very weak or tired
- you have unusual (not normal) muscle pain
- you have trouble breathing
- you have stomach pain with nausea and vomiting
- you feel cold, especially in your arms and legs
- you feel dizzy or light-headed
- you have a fast or irregular heartbeat

3. Serious liver problems. Some people who have taken medicines like abacavir tablets have developed serious liver problems called hepatotoxicity, with liver enlargement (hepatomegaly) and fat in the liver (steatosis). Hepatomegaly with steatosis is a serious medical emergency that can cause death.

Call your healthcare provider right away if you get any of the following signs or symptoms of liver problems:

- your skin or the white part of your eyes turns yellow (jaundice)
- your urine turns dark
- your bowel movements (stools) turn light in color
- you don’t feel like eating food for several days or longer
- you feel sick to your stomach (nausea)
- you have lower stomach area (abdominal) pain

You may be more likely to get lactic acidosis or serious liver problems if you are female, very overweight, or have been taking nucleoside analogue medicines for a long time.

What is abacavir?

Abacavir is a prescription medicine used to treat HIV infection. Abacavir is a medicine called a nucleoside analogue reverse transcriptase inhibitor (NRTI). Abacavir is always used with other anti-HIV medicines. When used in combination with these other medicines, abacavir helps lower the amount of HIV in your blood.

- Abacavir does not cure HIV infection or AIDS.
- It is not known if abacavir will help you live longer or have fewer of the medical problems that people get with HIV or AIDS.
- It is very important that you see your doctor regularly while you are taking abacavir tablets.

Who should not take abacavir tablets?

Do not take abacavir tablets if you:

- are allergic to abacavir or any of the ingredients in abacavir tablets. See the end of this Medication Guide for a complete list of ingredients in abacavir tablets.
- have certain liver problems.

What should I tell my healthcare provider before taking abacavir tablets?

Before you take abacavir tablets, tell your healthcare provider if you:

- have been tested and know whether or not you have a particular gene variation called HLA-B*5701
- have hepatitis B virus infection or have other liver problems
- have heart problems, smoke, or have diseases that increase your risk of heart disease such as high blood pressure, high cholesterol, or diabetes.
- are pregnant or plan to become pregnant. It is not known if abacavir will harm your unborn baby. Talk to your healthcare provider if you are pregnant or plan to become pregnant.
- Pregnancy Registry. If you take abacavir tablets while you are pregnant, talk to your healthcare provider about how you can take part in the Pregnancy Registry for abacavir tablets. The purpose of the pregnancy registry is to collect information about the health of you and your baby.
- are breast-feeding or plan to breast-feed. Do not breast-feed. We do not know if abacavir can be passed to your baby in your breast milk and whether it could harm your baby. Also, mothers with HIV-1 should not breast-feed because HIV-1 can be passed to the baby in the breast milk.
- Tell your healthcare provider about all the medicines you take, including prescription and nonprescription medicines, vitamins, and herbal supplements.

Especially tell your healthcare provider if you take:

- alcohol
- methadone
- TRIZIVIR®** (abacavir sulfate, lamivudine, and zidovudine)
- EPZICOM®** (abacavir sulfate and lamivudine)

Ask your healthcare provider if you are not sure if you take one of the medicines listed above.

Abacavir tablets may affect the way other medicines work, and other medicines may affect how abacavir tablets work.

Know the medicines you take. Keep a list of your medicines with you to show to your healthcare provider and pharmacist when you get a new medicine.

How should I take abacavir tablets?

- Take abacavir exactly as your healthcare provider tells you to take it.
- Abacavir is taken by mouth as a tablet or a liquid.
- Abacavir tablets may be taken with or without food.
- Do not skip doses.
- Children aged 3 months and older can also take abacavir. The child’s healthcare provider will decide the right dose and whether the child should take the tablet or liquid, based on the child’s weight. The dose should not be more than the recommended adult dose.
- Do not let your abacavir tablets run out. If you stop your anti-HIV medicines, even for a short time, the amount of virus in your blood may increase and the virus may become harder to treat. If you take too much abacavir, call your healthcare provider or poison control center or go to the nearest hospital emergency room right away.

What are the possible side effects of abacavir tablets?

- Abacavir tablets can cause serious side effects including allergic reactions, lactic acidosis, and liver problems. See “What is the most important information I should know about abacavir tablets?”
- Changes in immune system (Immune Reconstitution Syndrome). Your immune system may get stronger and begin to fight infections that have been hidden in your body for a long time. Tell your healthcare provider if you start having new or worse symptoms of infection after you start taking abacavir tablets.
- Changes in body fat (fat redistribution). Changes in body fat (lipoatrophy or lipodystrophy) can happen in some people taking antiretroviral medicines including abacavir tablets.

These changes may include:

- more fat in or around your trunk, upper back and neck (buffalo hump), breast, or chest
- loss of fat in your legs, arms, or face
- Heart attack (myocardial infarction). Some HIV medicines including abacavir tablets may increase your risk of heart attack.

The most common side effects of abacavir in adults include:

- bad dreams or sleep problems
- nausea
- headache
- tiredness
- vomiting

The most common side effects of abacavir in children include:

- fever and chills
- nausea
- vomiting
- rash
- ear, nose, or throat infections

Tell your healthcare provider if you have any side effect that bothers you or that does not go away.

These are not all the possible side effects of abacavir tablets. For more information, ask your healthcare provider or pharmacist.

Call your doctor for medical advice about side effects. You may report side effects to FDA at 1-800-FDA-1088.

How should I store abacavir tablets?

- Store abacavir tablets at room temperature, at 20° to 25°C (68° to 77°F).
- Do not freeze abacavir tablets.
- Keep abacavir tablets and all medicines out of the reach of children.

General information for safe and effective use of abacavir tablets

Avoid doing things that can spread HIV-1 infection to others.

- Do not share needles or other injection equipment.
- Do not share personal items that can have blood or body fluids on them, like toothbrushes and razor blades.
- Do not have any kind of sex without protection. Always practice safe sex by using a latex or polyurethane condom to lower the chance of sexual contact with semen, vaginal secretions, or blood.

Medicines are sometimes prescribed for purposes other than those listed in a Medication Guide. Do not use abacavir for a condition for which it was not prescribed. Do not give abacavir tablets to other people, even if they have the same symptoms that you have. It may harm them.

This Medication Guide summarizes the most important information about abacavir tablets. If you would like more information, talk with your healthcare provider. You can ask your healthcare provider or pharmacist for the information that is written for healthcare professionals.

For more information call Mylan Pharmaceuticals Inc. at 1-877-4-INFO-RX (1-877-446-3679).

What are the ingredients in abacavir tablets?

Active ingredient: abacavir sulfate, USP

Inactive ingredients: colloidal silicon dioxide, hypromellose, magnesium stearate, microcrystalline cellulose, polyethylene glycol, red iron oxide, sodium starch glycolate, titanium dioxide and yellow iron oxide.

This Medication Guide has been approved by the US Food and Drug Administration.

** The brand names mentioned are registered trademarks of their respective manufacturers.
Manufactured for:
Mylan Pharmaceuticals Inc.
Morgantown, WV 26505 U.S.A.

Manufactured in India by:
Mylan Laboratories Limited
Hyderabad — 500 034, India
Code No.: MH/DRUGS/25/NKD/89

This Product was Repackaged By:

State of Florida DOH Central Pharmacy
104-2 Hamilton Park Drive
Tallahassee, FL 32304
United States

PACKAGE LABEL

PRINCIPAL DISPLAY PANEL - 300 mg

NDC 53808-0627-1

Abacavir
Tablets, USP
300 mg

Notice to Authorized Dispenser:
Each time abacavir tablets are dispensed,
give the patient a Medication Guide and
Warning Card from the carton.

Rx only 30 Tablets

Each film-coated tablet contains
abacavir sulfate, USP equivalent to
300 mg of abacavir.

Usual Dosage: See accompanying
prescribing information.

Keep this and all medication out of the
reach of children.

Store at 20° to 25°C (68° to 77°F). [See
USP Controlled Room Temperature.]